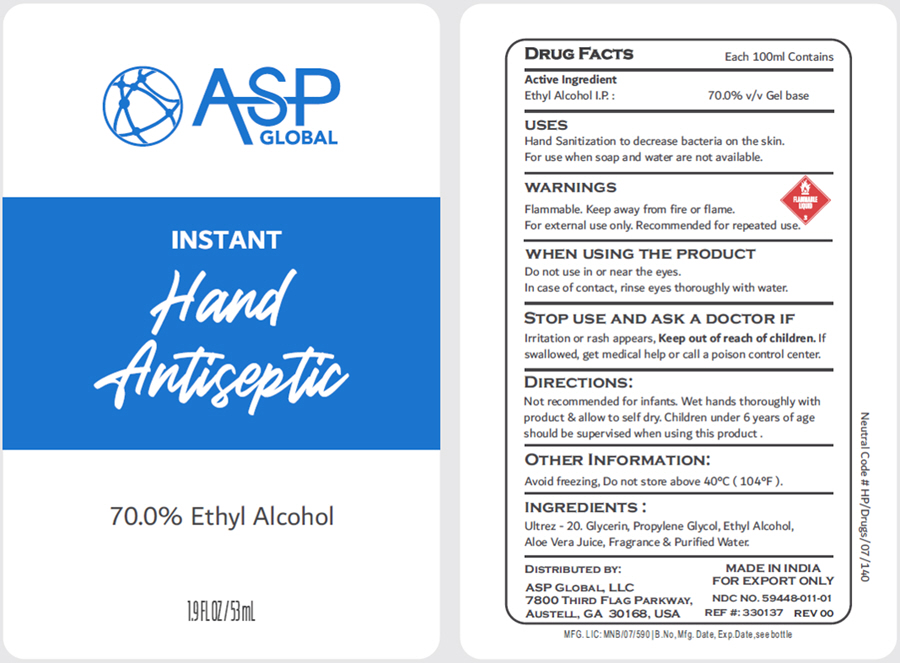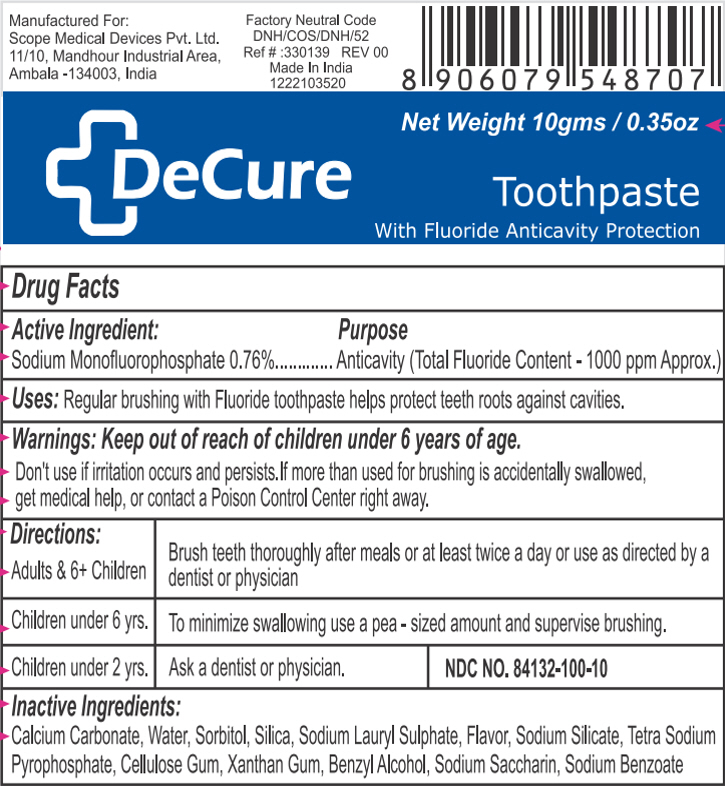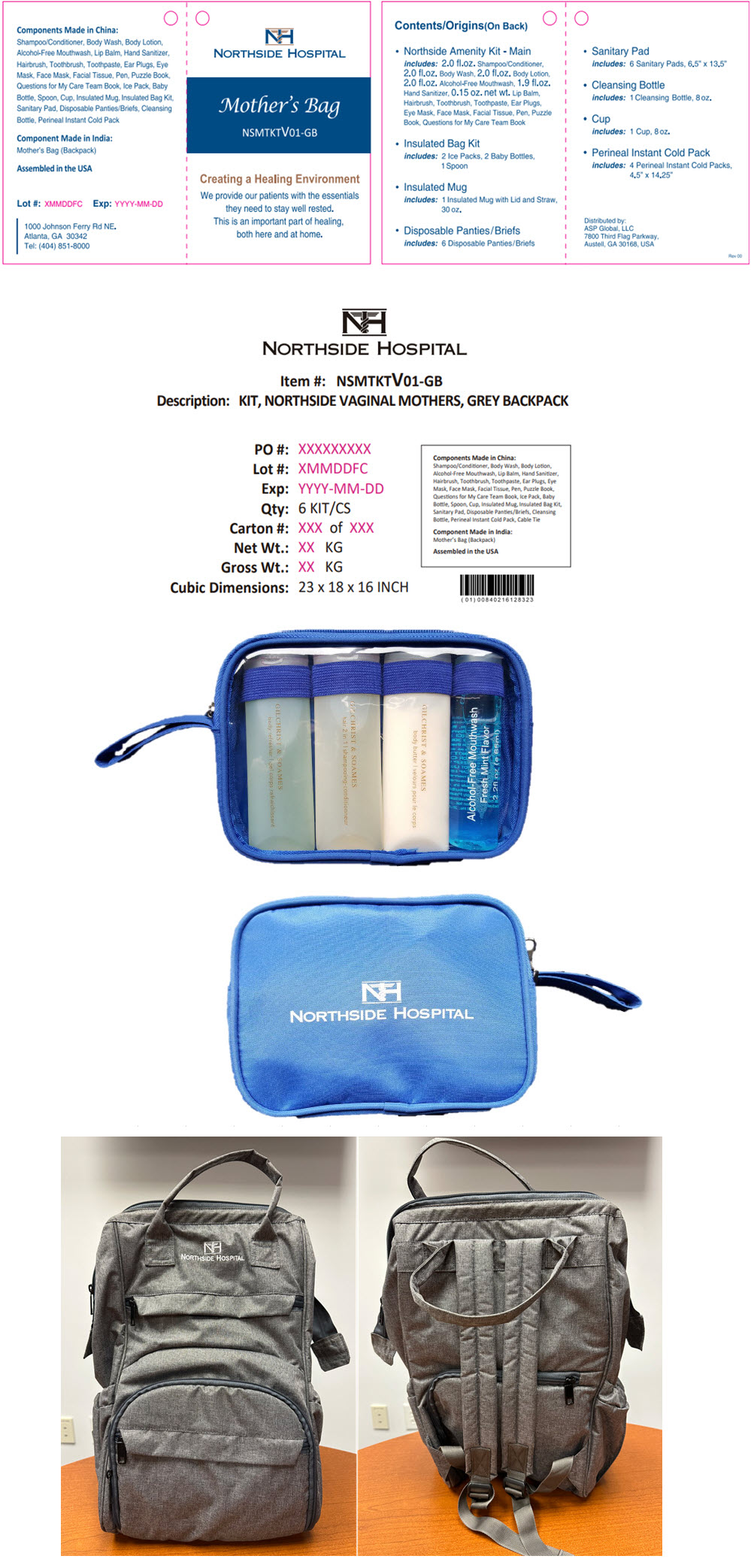 DRUG LABEL: Northside Hospital Mothers Kit, Grey Backpack
NDC: 59448-214 | Form: KIT | Route: TOPICAL
Manufacturer: ASP Global, LLc
Category: otc | Type: HUMAN OTC DRUG LABEL
Date: 20250929

ACTIVE INGREDIENTS: ALCOHOL 70 mL/100 mL; SODIUM MONOFLUOROPHOSPHATE 7.6 mg/1 g
INACTIVE INGREDIENTS: Water; Aloe Vera Leaf; Glycerin; Propylene Glycol; ACRYLATES/C10-30 ALKYL ACRYLATE CROSSPOLYMER (60000 MPA.S AT 0.5%); FRAGRANCE 13576; CALCIUM CARBONATE; Water; Sorbitol; Sodium Lauryl Sulfate; SODIUM PYROPHOSPHATE; SACCHARIN SODIUM; SILICON DIOXIDE; SODIUM SILICATE; CARBOXYMETHYLCELLULOSE SODIUM, UNSPECIFIED; XANTHAN GUM; BENZYL ALCOHOL; Sodium Benzoate; METHYL SALICYLATE

Northside Hospital Mothers Kit, Grey Backpack

Instant Hand Antiseptic

DRUG FACTS

Active Ingredient

Ethyl Alcohol I.P. :

PURPOSE

70.0% v/v Gel base

USES

Hand Sanitization to decrease bacteria on the skin.

For use when soap and water are not available.

WARNINGS

Flammable. Keep away from fire or flame.

For external use only. Recommended for repeated use.

WHEN USING THE PRODUCT

Do not use in or near the eyes.

In case of contact, rinse eyes thoroughly with water.

STOP USE AND ASK A DOCTOR IF

Irritation or rash appears,

Keep out of reach of children. If swallowed, get medical help or call a poison control center.

DIRECTIONS

Not recommended for infants. Wet hands thoroughly with product & allow to self dry. Children under 6 years of age should be supervised when using this product.

OTHER INFORMATION

Avoid freezing, Do not store above 40°C (104°F).

INGREDIENTS

Ultrez - 20. Glycerin, Propylene Glycol, Ethyl Alcohol, Aloe Vera Juice, Fragrance & Purified Water.

DISTRIBUTED BY:

ASP GLOBAL, LLC
7800 THIRD FLAG PARKWAY,
AUSTELL, GA 30168, USA

DeCure Toothpaste

Drug Facts

Active Ingredient

Sodium Monofluorophosphate 0.76%

Purpose

Anticavity (Total Fluoride Content - 1000 ppm Approx.)

Uses

Regular brushing with Fluoride toothpaste helps protect teeth roots against cavities.

Warnings

Keep out of reach of children under 6 years of age.

DO NOT USE

Don't use if irritation occurs and persists. If more than used for brushing is accidentally swallowed, get medical help, or contact a Poison Control Center right away.

Directions

Adults & 6+ Children | Brush teeth thoroughly after meals or at least twice a day or use as directed by a dentist or physician
Children under 6 yrs. | To minimize swallowing use a pea - sized amount and supervise brushing.
Children under 2 yrs. | Ask a dentist or physician. | NDC NO. 84132-100-10

Inactive Ingredients

Calcium Carbonate, Water, Sorbitol, Silica, Sodium Lauryl Sulphate, Flavor, Sodium Silicate, Tetra Sodium Pyrophosphate, Cellulose Gum, Xanthan Gum, Benzyl Alcohol, Sodium Saccharin, Sodium Benzoate

PRINCIPAL DISPLAY PANEL - 53 mL Bottle Label

ASP
GLOBAL

INSTANT
Hand
Antiseptic

70.0% Ethyl Alcohol

1.9 FL OZ / 53 mL

PRINCIPAL DISPLAY PANEL - 10 gms Tube Label

DeCure

Net Weight 10gms / 0.35oz

Toothpaste

With Fluoride Anticavity Protection

PRINCIPAL DISPLAY PANEL - Kit Label

NORTHSIDE HOSPITAL

Mother's Bag
NSMTKTV01-GB

Creating a Healing Environment
We provide our patients with the essentials
they need to stay well rested.
This is an important part of healing,
both here and at home.

Contents/Origins(On Back)

- Northside Amenity Kit - Main
  includes: 2.0 fl.oz. Shampoo/Conditioner,
  2.0 fl.oz. Body Wash, 2.0 fl.oz. Body Lotion,
  2.0 fl.oz. Alcohol-free Mouthwash, 1.9 fl.oz.
  Hand Sanitizer, 0.15 oz. net wt. Lip Balm,
  Hairbrush, Toothbrush, Toothpaste, Ear Plugs,
  Eye Mask, Face Mask, Facial Tissue, Pen, Puzzle
  Book, Questions for My Care Team Book
- Insulated Bag Kit
  includes: 2 Ice Packs, 2 Baby Bottles,
  1 Spoon
- Insulated Mug
  includes: 1 Insulated Mug with Lid and Straw,
  30 oz.
- Disposable Panties/Briefs
  includes: 6 Disposable Panties/ Briefs
- Sanitary Pad
  includes: 6 Sanitary Pads, 6.5" x 13.5"
- Cleansing Bottle
  includes: 1 Cleansing Bottle, 8 oz.
- Cup
  includes: 1 Cup, 8 oz.
- Perineal Instant Cold Pack
  Includes: 4 Perineal Instant Cold Packs,
  4.5" x 14.25"

Distributed by:
ASP Global, LLC
7800 Third Flag Parkway,
Austell, GA 30168, USA

REV 00

Components Made in China:

Shampoo/Conditioner, Body Wash, Body Lotion,
Alcohol-Free Mouthwash, Lip Balm, Hand Sanitizer,
Hairbrush, Toothbrush, Toothpaste, Ear Plugs, Eye
Mask, Face Mask, Facial Tissue, Pen, Puzzle Book,
Questions for My Care Team Book, Ice Pack, Baby
Bottle, Spoon, Cup, Insulated Mug, Insulated Bag Kit,
Sanitary Pad, Disposable Panties/Briefs, Cleansing
Bottle, Perineal Instant Cold Pack

Component Made in India:
Mother's Bag (Backpack)

Assembled in the USA

Lot #: XMMDDFC
Exp: YYYY-MM-DD

1000 Johnson Ferry Rd NE.
Atlanta, GA 30342
Tel: (404) 851-8000

NORTHSIDE HOSPITAL

Item #: NSMTKTV01-GB

Description: KIT, NORTHSIDE VAGINAL MOTHERS, GREY BACKPACK

PO #: XXXXXXXXX
Lot #: XMMDDFC
Exp: YYYY-MM-DD
Qty: 6 KIT/CS
Carton #: XXX of XXX
Net Wt.: XX KG
Gross Wt.: XX KG
Cubic Dimensions: 23 x 18 x 16 INCH

Components Made in China:

Shampoo/Conditioner, Body Wash, Body Lotion,
Alcohol-Free Mouthwash, Lip Balm, Hand Sanitizer,
Hairbrush, Toothbrush, Toothpaste, Ear Plugs, Eye
Mask, Face Mask, Facial Tissue, Pen, Puzzle Book,
Questions for My Care Team Book, Ice Pack, Baby
Bottle, Spoon, Cup, Insulated Bag Kit,
Sanitary Pad, Disposable Panties/Briefs, Cleansing
Bottle, Perineal Instant Cold Pack, Cable Tie

Components Made in India:
Mother's Bag (Backpack)

Assembled in the USA

NORTHSIDE HOSPITAL

NORTHSIDE HOSPITAL